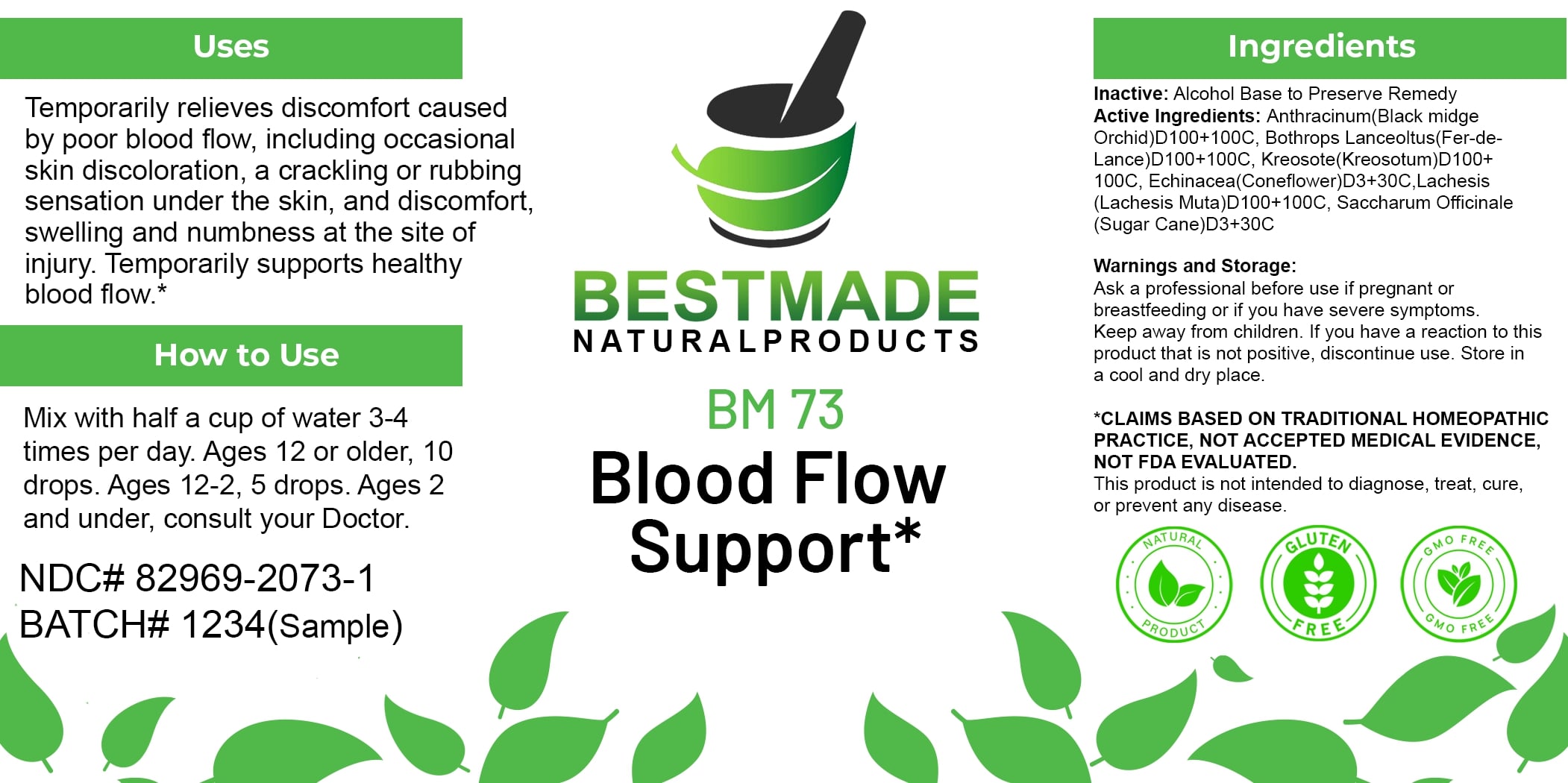 DRUG LABEL: Bestmade Natural Products BM73
NDC: 82969-2073 | Form: LIQUID
Manufacturer: Bestmade Natural Products
Category: homeopathic | Type: HUMAN OTC DRUG LABEL
Date: 20250130

ACTIVE INGREDIENTS: BOTHROPS ATROX VENOM 30 [hp_C]/30 [hp_C]; SUCROSE 30 [hp_C]/30 [hp_C]; LACHESIS MUTA VENOM 30 [hp_C]/30 [hp_C]; ECHINACEA, UNSPECIFIED 30 [hp_C]/30 [hp_C]; BACILLUS ANTHRACIS IMMUNOSERUM RABBIT 30 [hp_C]/30 [hp_C]; WOOD CREOSOTE 30 [hp_C]/30 [hp_C]
INACTIVE INGREDIENTS: ALCOHOL 30 [hp_C]/30 [hp_C]

BM73

DOSAGE AND ADMINISTRATION

How to Use

Mix with half a cup of water 3-4 times per day. Ages 12 or older, 10 drops. Ages 12-2, 5 drops. Ages 2 and under, consult your Doctor.

INACTIVE INGREDIENT

Ingredients

Inactive: Alcohol Base to Preserve Remedy

ACTIVE INGREDIENT

Active Ingredients: Anthracinum(Black midge Orchid)D100+100C, Bothrops Lanceolatus(Fer-de-Lance)D100+100C, Kreosotum(Kreosotum)D100+100C, Echinacea(Coneflower)D3+30C, Lachesis (Lachesis Muta)D100+100C, Saccharum Officinale (Sugar Cane)D3+30C

Uses

Temporarily relieves discomfort caused by poor blood flow, including occasional skin discoloration, a crackling or rubbing sensation under the skin, and discomfort, swelling and numbness at the site of injury. Temporarily supports healthy blood flow.*

*CLAIMS BASED ON TRADITIONAL HOMEOPATHIC PRACTICE, NOT ACCEPTED MEDICAL EVIDENCE, NOT FDA EVALUATED.

This product is not intended to diagnose, treat, cure, or prevent any disease.

Uses

Temporarily relieves discomfort caused by poor blood flow, including occasional skin discoloration, a crackling or rubbing sensation under the skin, and discomfort, swelling and numbness at the site of injury. Temporarily supports healthy blood flow.*

*CLAIMS BASED ON TRADITIONAL HOMEOPATHIC PRACTICE, NOT ACCEPTED MEDICAL EVIDENCE, NOT FDA EVALUATED.

This product is not intended to diagnose, treat, cure, or prevent any disease.

KEEP OUT OF REACH OF CHILDREN

Warnings and Storage:

Ask a professional before use if pregnant or breastfeeding or if you have severe symptoms. Keep away from children. If you have a reaction to this product that is not positive, discontinue use. Store in a cool and dry place.

Warnings and Storage:

Ask a professional before use if pregnant or breastfeeding or if you have severe symptoms. Keep away from children. If you have a reaction to this product that is not positive, discontinue use. Store in a cool and dry place.

*CLAIMS BASED ON TRADITIONAL HOMEOPATHIC PRACTICE, NOT ACCEPTED MEDICAL EVIDENCE, NOT FDA EVALUATED.

This product is not intended to diagnose, treat, cure, or prevent any disease.

Entire package label